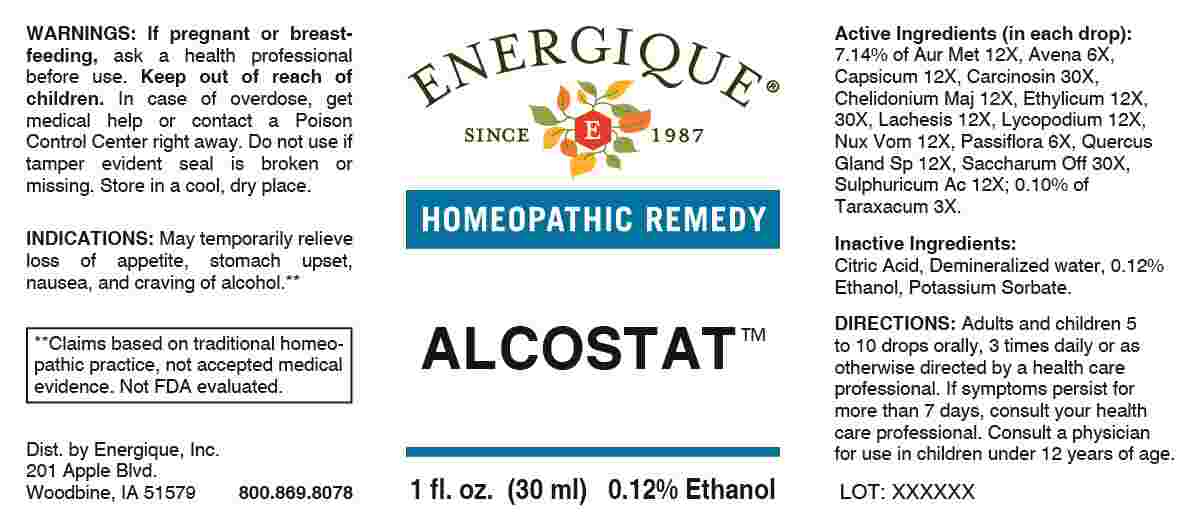 DRUG LABEL: Alcostat
NDC: 44911-0735 | Form: LIQUID
Manufacturer: Energique, Inc.
Category: homeopathic | Type: HUMAN OTC DRUG LABEL
Date: 20250227

ACTIVE INGREDIENTS: TARAXACUM OFFICINALE 3 [hp_X]/1 mL; AVENA SATIVA FLOWERING TOP 6 [hp_X]/1 mL; PASSIFLORA INCARNATA FLOWERING TOP 6 [hp_X]/1 mL; GOLD 12 [hp_X]/1 mL; CAPSICUM 12 [hp_X]/1 mL; CHELIDONIUM MAJUS WHOLE 12 [hp_X]/1 mL; LACHESIS MUTA VENOM 12 [hp_X]/1 mL; LYCOPODIUM CLAVATUM SPORE 12 [hp_X]/1 mL; STRYCHNOS NUX-VOMICA SEED 12 [hp_X]/1 mL; QUERCUS ROBUR NUT 12 [hp_X]/1 mL; SULFURIC ACID 12 [hp_X]/1 mL; ALCOHOL 12 [hp_X]/1 mL; HUMAN BREAST TUMOR CELL 30 [hp_X]/1 mL; SUCROSE 30 [hp_X]/1 mL
INACTIVE INGREDIENTS: ANHYDROUS CITRIC ACID; POTASSIUM SORBATE; WATER

DRUG FACTS:

ACTIVE INGREDIENTS:

(in each drop): 7.14% Aurum Metallicum 12X, Avena Sativa 6X, Capsicum Annuum 12X, Carcinosin 30X, Chelidonium Majus 12X, Ethylicum 12X, 30X, Lachesis Mutus 12X, Lycopodium Clavatum 12X, Nox Vomica 12X, Passiflora Incarnata 6X, Quercus Glandium Spiritus 12X, Saccharum Officinale 30X, Sulphuricum Acidum 12X; 0.10% of Taraxacum Officinale 3X.

PURPOSE:

May temporarily relieve loss of appetite, stomach upset, nausea, and craving of alcohol.**

**Claims based on traditional homeopathic practice, not accepted medical evidence. Not FDA evaluated.

WARNINGS:

If pregnant or breast-feeding, ask a health professional before use.

Keep out of reach of children. In case of overdose, get medical help or contact a Poison Control Center right away.

Do not use if tamper evident seal is broken or missing. Store in a cool, dry place.

KEEP OUT OF REACH OF CHILDREN:

In case of overdose, get medical help or contact a Poison Control Center right away.

DIRECTIONS:

Adults and children 5 to 10 drops orally, 3 times daily or as otherwise directed by a health care professional. If symptoms persist for more than 7 days, consult your health care professional. Consult a physician for use in children under 12 years of age.

INDICATIONS:

May temporarily relieve loss of appetite, stomach upset, nausea, and craving of alcohol.**

**Claims based on traditional homeopathic practice, not accepted medical evidence. Not FDA evaluated.

INACTIVE INGREDIENTS:

Citric Acid, Demineralized Water, 0.12% Ethanol, Potassium Sorbate.

QUESTIONS:

Dist. by Energique, Inc.

201 Apple Blvd

Woodbine, IA 51579

800.869.8078

PACKAGE LABEL DISPLAY:

ENERGIQUE

SINCE 1987

HOMEOPATHIC REMEDY

ALCOSTAT

1 fl. oz. (30 ml)